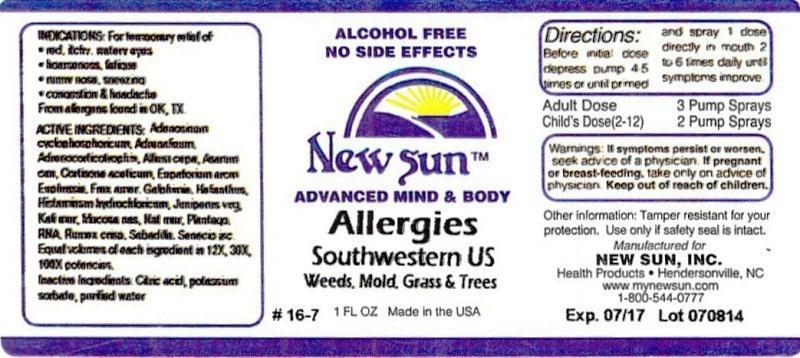 DRUG LABEL: Allergies Total Mold Control
NDC: 66579-0036 | Form: LIQUID
Manufacturer: New Sun Inc.
Category: homeopathic | Type: HUMAN OTC DRUG LABEL
Date: 20140804

ACTIVE INGREDIENTS: ADENOSINE CYCLIC PHOSPHATE 12 [hp_X]/29 mL; EPINEPHRINE 12 [hp_X]/29 mL; ONION 12 [hp_X]/29 mL; CORTICOTROPIN 12 [hp_X]/29 mL; ASARUM CANADENSE ROOT 12 [hp_X]/29 mL; CORTISONE ACETATE 12 [hp_X]/29 mL; AGERATINA AROMATICA ROOT 12 [hp_X]/29 mL; EUPHRASIA STRICTA 12 [hp_X]/29 mL; FRAXINUS AMERICANA BARK 12 [hp_X]/29 mL; GALPHIMIA GLAUCA FLOWERING TOP 12 [hp_X]/29 mL; HELIANTHUS ANNUUS FLOWERING TOP 12 [hp_X]/29 mL; HISTAMINE DIHYDROCHLORIDE 12 [hp_X]/29 mL; JUNIPERUS VIRGINIANA TWIG 12 [hp_X]/29 mL; POTASSIUM CHLORIDE 12 [hp_X]/29 mL; SUS SCROFA NASAL MUCOSA 12 [hp_X]/29 mL; SODIUM CHLORIDE 12 [hp_X]/29 mL; PLANTAGO MAJOR 12 [hp_X]/29 mL; SACCHAROMYCES CEREVISIAE RNA 12 [hp_X]/29 mL; RUMEX CRISPUS ROOT 12 [hp_X]/29 mL; SCHOENOCAULON OFFICINALE SEED 12 [hp_X]/29 mL; JACOBAEA VULGARIS 12 [hp_X]/29 mL
INACTIVE INGREDIENTS: CITRIC ACID MONOHYDRATE; POTASSIUM SORBATE; WATER

Allergies Southwestern US

DOSAGE AND ADMINISTRATION

Directions: Before initial dose depress pump 4-5 times or until primed and spray 1 dose directly in mouth 2 to 6 times daily until symptoms improve.

Adult Dose: 3 Pump Sprays

Child's Dose (2-12): 2 Pump Sprays

WARNINGS

Warnings: If symptoms persist or worsen, seek advice of physician. If pregnant or breast-feeding, take only on advice of physician.

Keep out of reach of children.

Other information: Tamper resistant for your protection. Use only if safety seal is intact.

PURPOSE

Indications: For temporary relief of: •red, itchy, watery eyes •hoarseness, fatigue •runny nose, sneezing •congestion and headache

From allergens found in OK, TX

ACTIVE INGREDIENT

Active Ingredients: Adenosinum cyclophosphoricum, Adrenalinum, Adrenocorticotrophin, Allium cepa, Asarum canadense, Cortisone aceticum, Eupatorium aromaticum, Euphrasia officinalis, Fraxinus americana, Galphimia glauca, Helianthus annuus, Histaminum hydrochloricum, Juniperus virginiana, Kali muriaticum, Mucosa nasalis suis, Natrum muriaticum, Plantago major, RNA, Rumex crispus, Sabadilla, Senecio jacobaea. Equal volumes of each ingredient in 12X, 30X, 100X potencies.

Inactive Ingredient: Citric acid, potassium sorbate, purified water.

INDICATIONS AND USAGE

Indications: For temporary relief of: From allergens found in OK, TX

- red, itchy, watery eyes
- hoarseness, fatigue
- runny nose, sneezing
- congestion and headache

From allergens found in OK, TX